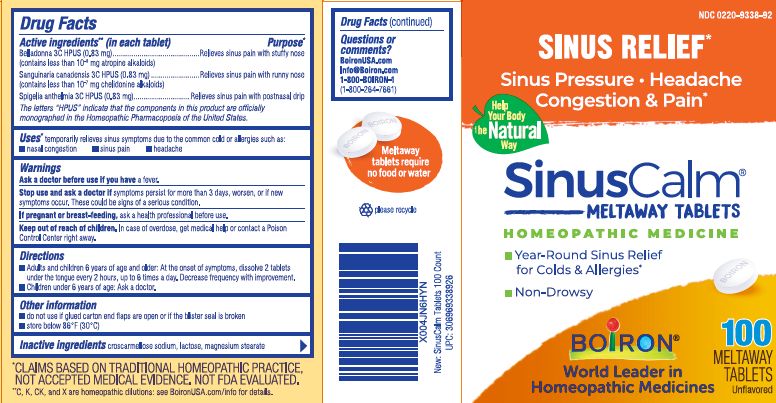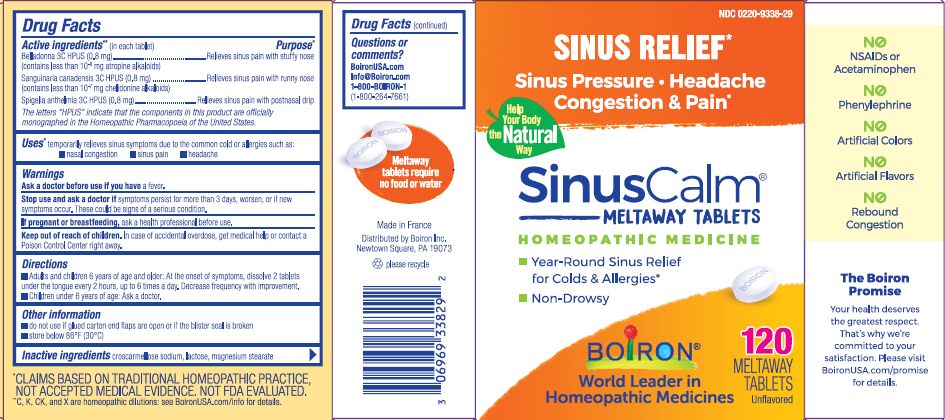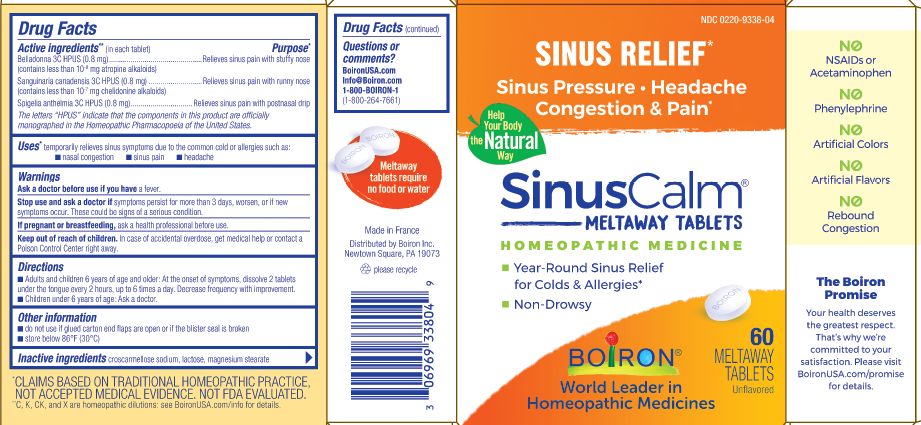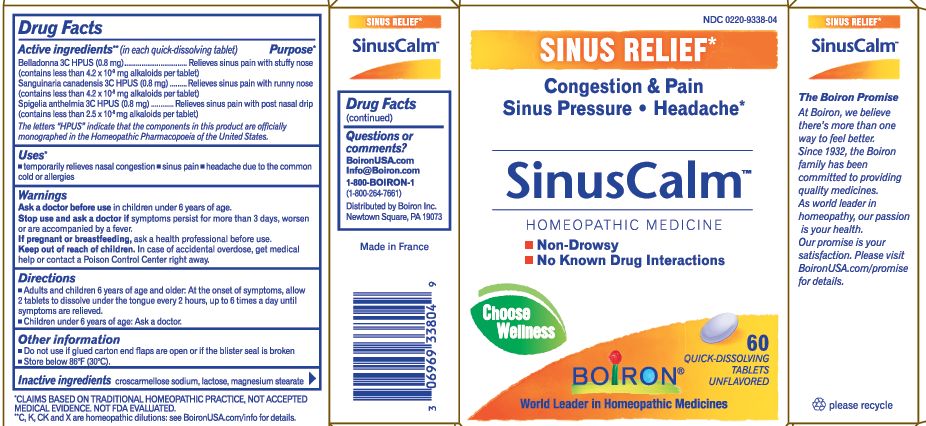 DRUG LABEL: SINUSCALM
NDC: 0220-9338 | Form: TABLET
Manufacturer: BOIRON
Category: homeopathic | Type: HUMAN OTC DRUG LABEL
Date: 20250320

ACTIVE INGREDIENTS: ATROPA BELLADONNA 3 [hp_C]/1 1; SANGUINARIA CANADENSIS ROOT 3 [hp_C]/1 1; SPIGELIA ANTHELMIA 3 [hp_C]/1 1
INACTIVE INGREDIENTS: LACTOSE, UNSPECIFIED FORM; CROSCARMELLOSE SODIUM; MAGNESIUM STEARATE

SINUSCALM

Active ingredients** (in each tablet)

Belladonna 3C HPUS (0.83 mg)(contains less than 10^-8 mg atropine alkaloids)

Sanguinaria canadensis 3C HPUS (0.83 mg)(contains less than 10^-7 mg chelidonine alkaloids)

Spigelia anthelmia 3C HPUS (0.83 mg)

The letters “HPUS” indicate that the components in this product are officially monographed in the Homeopathic Pharmacopoeia of the United States.

Purpose*

Belladonna 3C HPUS (0.83 mg)…Relieves sinus pain with stuffy nose

Sanguinaria canadensis 3C HPUS (0.83 mg)…Relieves sinus pain with runny nose

Spigelia anthelmia 3C HPUS (0.83 mg)…Relieves sinus pain with postnasal drip

Uses*

temporarily relieves sinus symptoms due to the common cold or allergies such as: ▪ nasal congestion ▪ sinus pain ▪ headache

Ask a doctor before use if you have a fever.

Stop use and ask a doctor if symptoms persist for more than 3 days, worsen, or if new symptoms occur. These could be signs of a serious condition.

PREGNANCY OR BREAST FEEDING

If pregnant or breast-feeding, ask a health professional before use.

Keep out of reach of children. In case of accidental overdose, get medical help or contact a Poison Control Center right away.

DOSAGE AND ADMINISTRATION

Adults and children 6 years of age and older: At the onset of symptoms, dissolve 2 tablets under the tongue every 2 hours, up to 6 times a day. Decrease frequency with improvement.

Children under 6 years of age: Ask a doctor.

do not use if glued carton end flaps are open or if the blister seal is broken.

Store below 86° F (30° C)

60 Meltaway Tablets unflavored

100 Meltaway Tablets unflavored

120 Meltaway Tablets unflavored

Sinus Relief*

Sinus Pressure, Headache, Congestion & Pain*

Year-Round Sinus Relief for Colds & Allergies*

Non-Drowsy

*CLAIMS BASED ON TRADITIONAL HOMEOPATHIC PRACTICE NOT ACCEPTED MEDICAL EVIDENCE. NOT FDA EVALUATED.
*C,K,CK, and X are homeopathic dilutions: see BoironUSA.com/info for details.

INACTIVE INGREDIENT

croscarmellose sodium, lactose, magnesium stearate

Questions or comments?

BoironUSA.com

Info@Boiron.com

1-800-BOIRON-1 (1-800-264-7661)

Made in France

Distributed by Boiron Inc.

Newtown Square, PA 19073